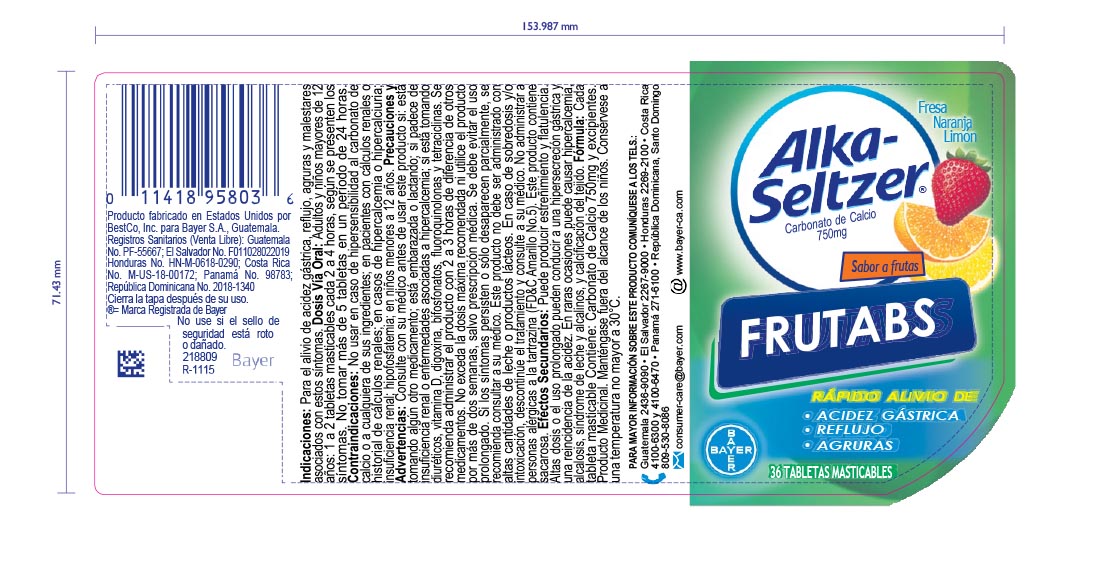 DRUG LABEL: Alka-Seltzer
NDC: 0280-0154 | Form: TABLET, CHEWABLE
Manufacturer: Bayer Healthcare LLC
Category: otc | Type: HUMAN OTC DRUG LABEL
Date: 20260108

ACTIVE INGREDIENTS: CALCIUM CARBONATE 750 mg/1 1
INACTIVE INGREDIENTS: MEDIUM-CHAIN TRIGLYCERIDES; SORBIC ACID; WHITE WAX; SORBITOL; RAW SUGAR; TITANIUM DIOXIDE; FD&C BLUE NO. 1; FD&C RED NO. 40; FD&C YELLOW NO. 5; FD&C YELLOW NO. 6; CARNAUBA WAX; WATER; METHYLPARABEN; SHELLAC; CORN SYRUP; MODIFIED CORN STARCH (1-OCTENYL SUCCINIC ANHYDRIDE); SODIUM BENZOATE; CITRIC ACID MONOHYDRATE; CARMINIC ACID; PHOSPHORIC ACID; PROPYLENE GLYCOL; PROPYLPARABEN; HYDROGENATED COCONUT OIL

Alka Seltzer Frutabs